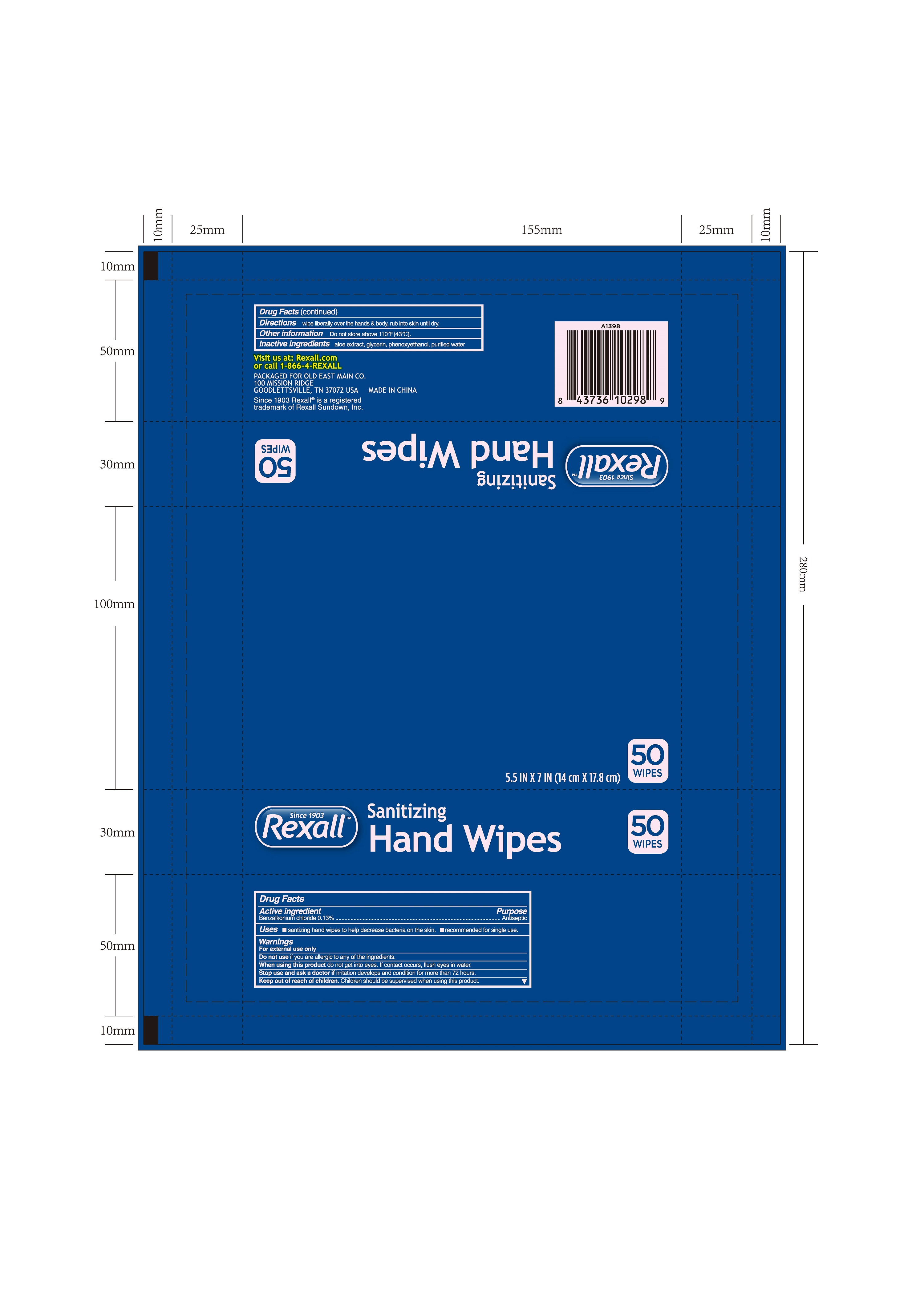 DRUG LABEL: HAND SANITIZE WIPES
NDC: 51706-958 | Form: CLOTH
Manufacturer: Landy International
Category: otc | Type: HUMAN OTC DRUG LABEL
Date: 20220321

ACTIVE INGREDIENTS: BENZALKONIUM CHLORIDE 0.13 g/100 g
INACTIVE INGREDIENTS: PHENOXYETHANOL; GLYCERIN; WATER; ALOE VERA LEAF

51706-958 HAND SANITIZE WIPES 0.13% Benzalkonium chloride

Active Ingredient(s)

Benzalkonium Chloride 0.13%

Purpose

Antiseptic

Use

Uses santizing hand wipes to help decrease bacteria on the skin.recommended for single use.

Warnings

For external use only
Do not use if you are allergic to any of the ingredients.
When using this product do not get into eyes. If contact occurs, flush eyes in water.
stop use and ask a doctor if irritation develops and condition for more than 72 hours.

Keep out of reach of children. Children should be supervised when using this product.

Directions

Directions wipe liberally over the hands & body, rub into skin until

Other information

- Other information Do not store above 110°F(43℃).

Inactive ingredients

aloe extract, glycerin, phenoxyethanol, purified water